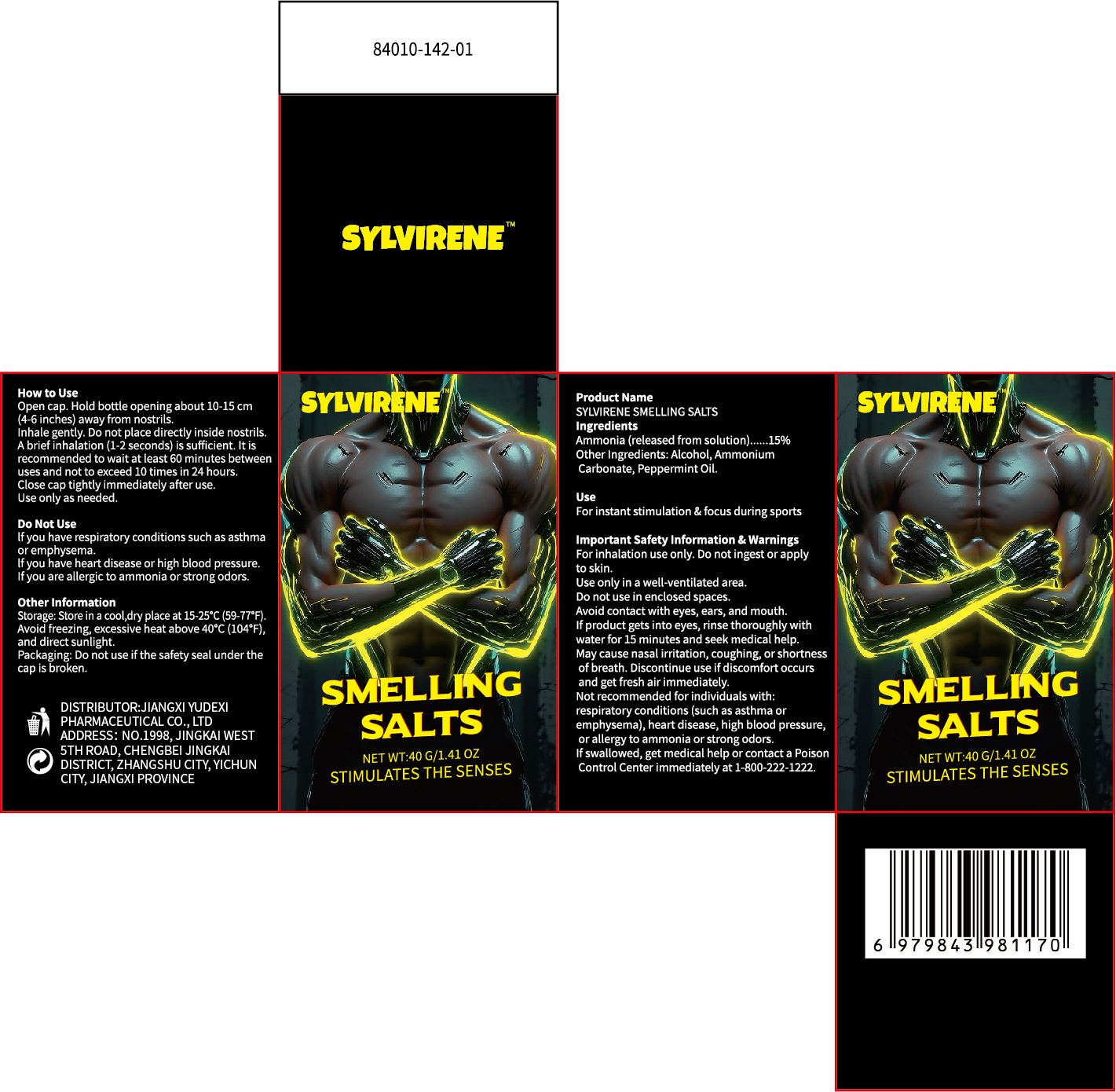 DRUG LABEL: SYLVIRENE SMELLING SALTS
NDC: 85248-140 | Form: INHALANT
Manufacturer: Jiangxi Yudexi Pharmaceutical Co., LTD
Category: otc | Type: HUMAN OTC DRUG LABEL
Date: 20260210

ACTIVE INGREDIENTS: AMMONIA 15 g/100 g
INACTIVE INGREDIENTS: AMMONIUM CARBONATE; ALCOHOL; PEPPERMINT OIL

85248-140

Active Ingredient

Ammonia (released from solution) 15%

Purpose

For instant stimulation & focus during sports

Use

For instant stimulation & focus during sports

Warnings

For inhalation use only. Do not ingest or apply to skin.
Use only in a well-ventilated area.
Do not use in enclosed spaces.
Avoid contact with eves. ears, and mouth.
If product gets into eyes, rinse thoroughly with
water for 15 minutes and seek medical help.
May cause nasal irritation, coughing, or shortness
of breath. Discontinue use if discomfort occurs
and get fresh air immediately.
Not recommended for individuals with:
respiratory conditions (such as asthma or
emphysema), heart disease, high blood pressure,
or allergy to ammonia or strong odors.

Do not use

If you have respiratory conditions such as asthma or emphysema.
If you have heart disease or high blood pressure.
If you are allergic to ammonia or strong odors.

When Using

Avoid contact with eves. ears, and mouth.
If product gets into eyes, rinse thoroughly with
water for 15 minutes and seek medical help.
May cause nasal irritation, coughing, or shortness
of breath. Discontinue use if discomfort occurs
and get fresh air immediately.

Stop Use

Not recommended for individuals with:
respiratory conditions (such as asthma or
emphysema), heart disease, high blood pressure,
or allergy to ammonia or strong odors.

Ask Doctor

Not recommended for individuals with:
respiratory conditions (such as asthma or
emphysema), heart disease, high blood pressure,
or allergy to ammonia or strong odors.

Keep Oot Of Reach Of Children

If swallowed, get medical help or contact a Poison Control Center immediately at 1-800-222-1222.

Directions

Hold bottle 10-15 cm (4-6 inches) from nostrils.
Inhale gently. Do not place directly inside the nostrils.
Do not inhale for more than 2 seconds per use.
Do not use more than once every 60 minutes.
Do not use more than 10 times per day.
Use only as needed. If symptoms persist, consult a healthcare professional.

Other information

Store in a cool, dry place at 15-25°C (59-77°F).
Avoid freezing, excessive heat above 40°C (104°F), and direct sunlight.
Do not use if safety seal under cap is broken .

Inactive ingredients

Alcohol, Cotton, Peppermint Oil.